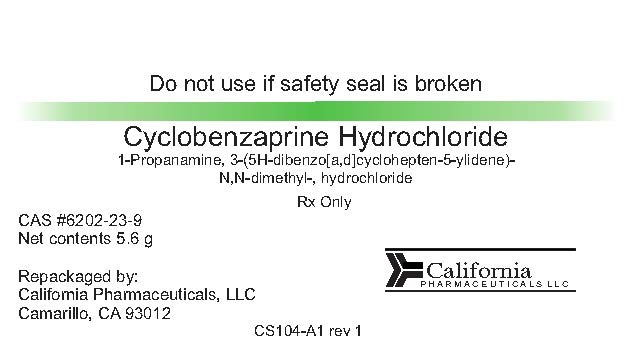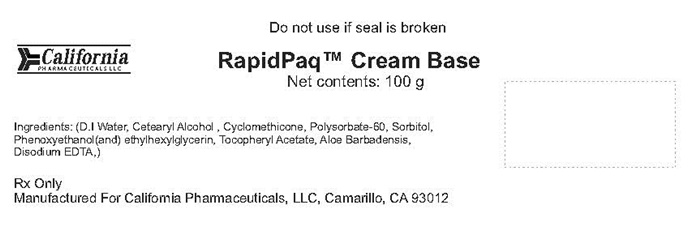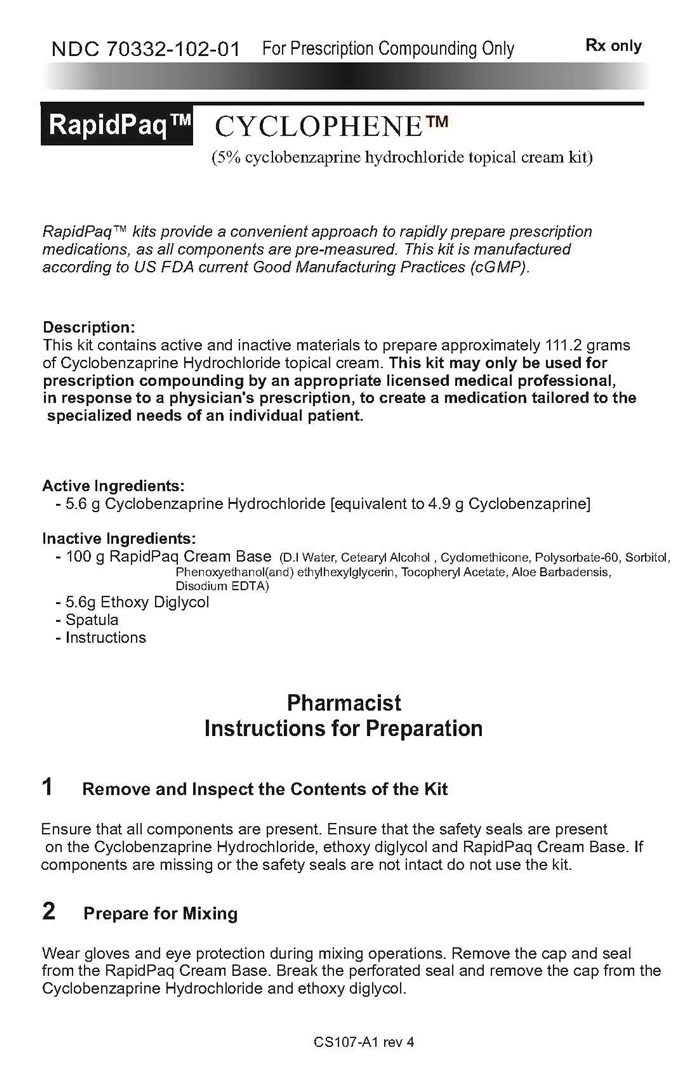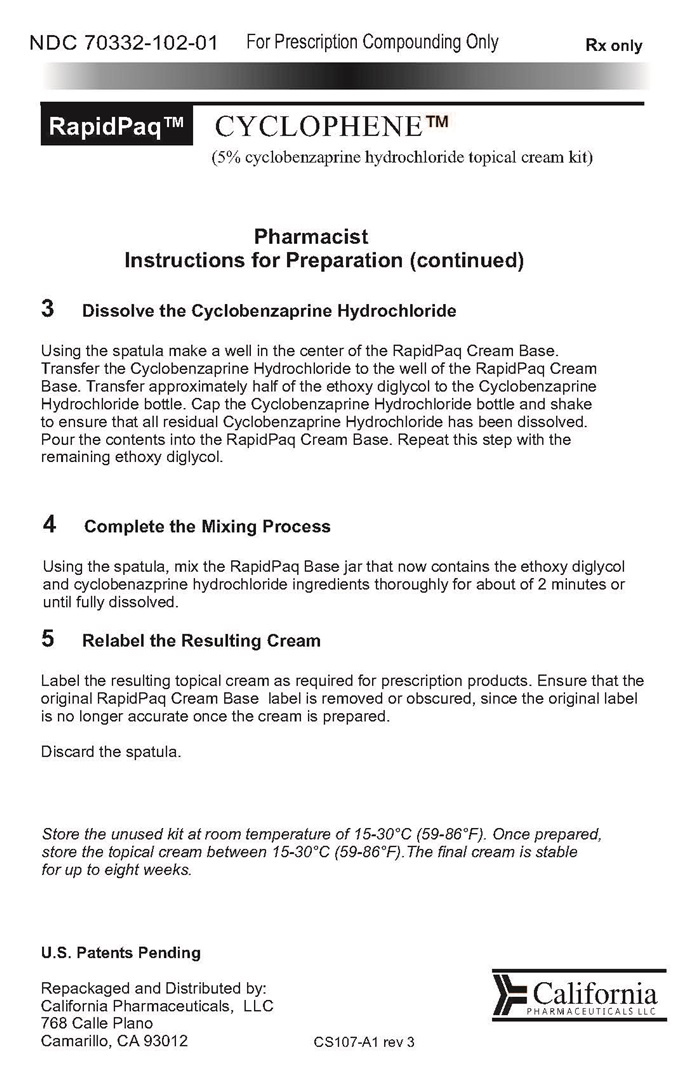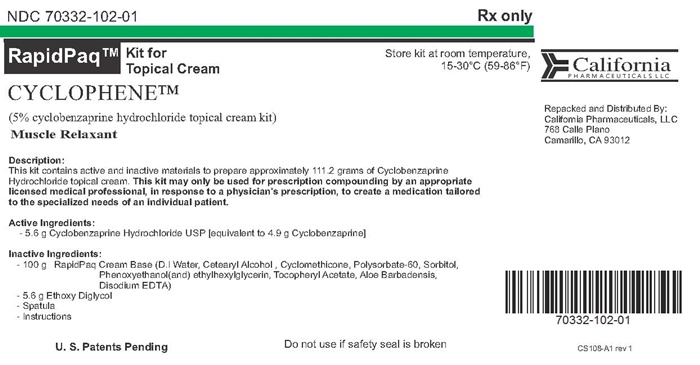 DRUG LABEL: CYCLOPHENE
NDC: 70332-102 | Form: KIT | Route: TOPICAL
Manufacturer: California Pharmaceuticals LLC
Category: prescription | Type: HUMAN PRESCRIPTION DRUG LABEL
Date: 20160725

ACTIVE INGREDIENTS: CYCLOBENZAPRINE HYDROCHLORIDE 5.6 g/5.6 g
INACTIVE INGREDIENTS: DIETHYLENE GLYCOL MONOETHYL ETHER; PHENOXYETHANOL; .ALPHA.-TOCOPHEROL ACETATE; CETOSTEARYL ALCOHOL; ETHYLHEXYLGLYCERIN; CYCLOMETHICONE 5; EDETATE DISODIUM; WATER; POLYSORBATE 60; SORBITOL; ALOE VERA LEAF

CYCLOPHENE - 70332-102

Instructions for Pharmacist Page 1 Page 2

NDC 70332-102-01

For Prescription Compounding Only

Rx only

RapidPaq™
CYCLOPHENE™
(5% cyclobenzaprine hydrochloride topical cream kit)

RapidPaq™ kits provide a convenient approach to rapidly prepare prescription medications, as all components are pre-measured. This kit is manufactured according to US FDA current Good Manufacturing Practices (cGMP).

Description:
This kit contains active and inactive materials to prepare approximately 111.2 grams of Cyclobenzaprine Hydrochloride topical cream. This kit may only be used for prescription compounding by an appropriate licensed medical professional, in response to a physician's prescription, to create a medication tailored to the specialized needs of an individual patient.

Active Ingredients:
- 5.6 g Cyclobenzaprine Hydrochloride [equivalent to 4.9 g Cyclobenzaprine]

Inactive Ingredients:
- 100 g RapidPaq Cream Base (D. l Water, Cetearyl Alcohol, Cyclomethicone, Polysorbate-60, Sorbitol, Phenoxyethanol(and)ethylhexylglycerin,
Tocopheryl Acetate, Aloe Barbadensis, Disodium EDTA)
- 5.6 Ethoxy Diglycol
- Spatula
- Instructions

Pharmacist Instructions for Preparation

1 Remove and Inspect the Contents of the Kit

Ensure that all components are present. Ensure that the safety seals are present on the Cyclobenzaprine Hydrochloride, ethoxy diglycol and RapidPaq Cream Base. If components are missing or the safety seals are not intact do not use the kit.

2 Prepare for Mixing

Wear gloves and eye protection during mixing operations. Remove the cap and seal from the RapidPaq Cream Base. Break the perforated seal and remove the cap from the Cyclobenzaprine Hydrochloride and ethoxy diglycol.

3 Dissolve the Cyclobenzaprine Hydrochloride

Using a spatula make a well in the center of the RapidPaq Cream Base. Transfer approximately half of the ethoxy diglycol to the Cyclobenzaprine Hydrochloride bottle. Cap the Cyclobenzaprine Hydrochloride bottle and shake to ensure that all residue Cyclobenzaprine Hydrochloride has been dissolved. Pour the contents into the RapidPaq Cream Base. Repeat this step with the remaining ethoxy diglycol.

4 Complete the Mixing Process

Using the spatula, mix the RapidPaq Base jar that now contains the ethoxy diglycol and cyclobenazprine hydrochloride ingredients thoroughly for about 2 minutes or until fully dissolved.

5 Relabel the Resulting Cream

Label the resulting topical cream as required for prescription products. Ensure that the original RapidPaq Cream Base label is removed or obscured, since the original label is no longer accurate once the cream is prepared.

Discard the spatula.

Store the unused kit at room temperature of 15-30°C (59-86°F). Once prepared, store the topical cream between 15-30°C (59-86°F). The final cream is stable for up to eight weeks.

U.S. Patents Pending

Repackaged and Distributed by:
California Pharmaceuticals, LLC
768 Calle Plano
Camarillo, CA 93012

California
PHARMACEUTICALS LLC

CS107-A1 rev 3

Cyclobenzaprine Hydrochloride product label

Do not use if saety seal is broken

Cyclobenzaprine Hydrochloride

1-propanamine, 3-(5H-dibenzo[a,d]cycloheptenn-5-ylidene)-N,N-dimethyl-, hydrochloride

RxOnly

CAS # 6202-23-9

Net contents 5.6 g

Repackaged by:

California Pharmaceuticals, LLC

Camarillo, CA 93012

California

PHARMACEUTICALS LLC

CS104-A1 rev 1

RapidPaq Cream Base product label

Do not use if seal is broken

RapidPaq™ Cream base

Net contents: 100 g

Ingredients: (D.l Water, Cetearyl Alcohol, Cyclomethicone, Polysorbate-60, Sorbitol, Phenoxyethanol(and)ethylhexylglycerin, Tocopheryl Acetate,

Aloe barbadensis, Disodium EDTA.)

RX Only

Manufactured for California Pharmaceyticals, LLC, Camarillo, CA 93012

CYCLOPHENE Kit product label

NDC 70332-102-01

Rx only

RapidPaq™

Kit for Topical Cream

CYCLOPHENE™

(5% cyclobenzaprine hydrochloride topical cream kit)

Muscle relaxant

Store at room temperature,

15-30°C (59-86°F)

Description:

This kit contains active and inactive materials to prepare approximately 111.2 grams of Cyclobenzaprine Hydrochloride topical cream. This kit may only be used for prescription compounding by an appropriate licensed medical professional, in response to a physician's prescription, to create a medication tailored to the specialized needs of an individual patient.

Active ingredient

- 5.6 g Cyclobenzaprine Hydrochloride USP [equivalent to 4.9 g Cyclobenzaprine]

Inactive Ingredients:

- 100 g RapidPaq Cream Base(D.l Water, Cetearyl Alcohol, Cyclomethicone, Polysorbate-60, Sorbitol, Phenoxyethanol(and) ethylhexylglycerin,

Tocopheryl Acetate, Aloe Barbadensis, Disodium EDTA)

- 5.6 g Ethoxy Diglycol

- Spatula

- Instructions

U.S. Patents Pending

Do not use if safety seal is broken

California

PHARMACEUTICALS LLC

Repacked and Distributed By;

Caifornis Pharmaceuticals, LLC

768 Calle Plano

Camarillo, CA 93012

CS 108-A1 rev 1